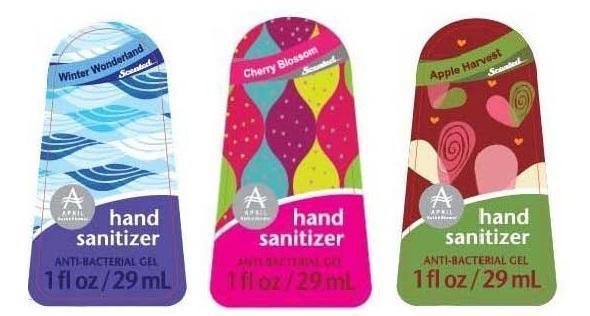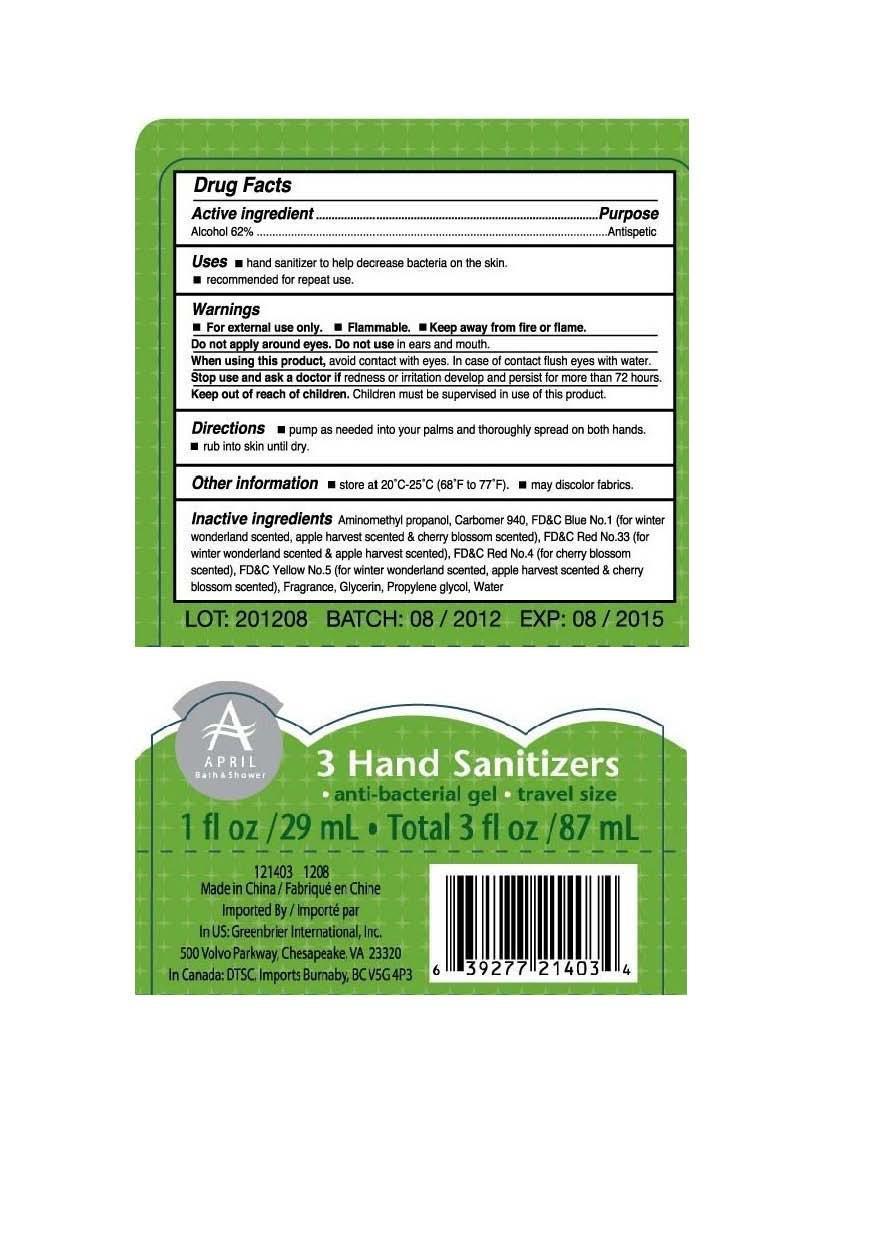 DRUG LABEL: 3 HAND SANITIZERS KIT
NDC: 33992-1500 | Form: KIT | Route: TOPICAL
Manufacturer: Greenbrier International, Inc. 
Category: otc | Type: HUMAN OTC DRUG LABEL
Date: 20120815

ACTIVE INGREDIENTS: Alcohol 62 mL/100 mL; Alcohol 62 mL/100 mL; Alcohol 62 mL/100 mL
INACTIVE INGREDIENTS: AMINOMETHYLPROPANOL; CARBOMER HOMOPOLYMER TYPE C (ALLYL PENTAERYTHRITOL CROSSLINKED); FD&C BLUE NO. 1; D&C RED NO. 33; FD&C YELLOW NO. 5; GLYCERIN; PROPYLENE GLYCOL; WATER; AMINOMETHYLPROPANOL; CARBOMER HOMOPOLYMER TYPE C (ALLYL PENTAERYTHRITOL CROSSLINKED); FD&C BLUE NO. 1; FD&C YELLOW NO. 5; GLYCERIN; PROPYLENE GLYCOL; WATER; FD&C RED NO. 4; AMINOMETHYLPROPANOL; CARBOMER HOMOPOLYMER TYPE C (ALLYL PENTAERYTHRITOL CROSSLINKED); FD&C BLUE NO. 1; D&C RED NO. 33; FD&C YELLOW NO. 5; GLYCERIN; PROPYLENE GLYCOL; WATER

Active ingredient
Ethyl Alcohol 62%

Purpose
Antiseptic

Uses

- hand sanitizer to help decrease bacteria on the skin.
- recommended for repeat use.

Warnings

- For external use only.
- Flammable.
- Keep away from fire or flame.

Do not apply around eyes. Do not use in ears and mouth.

When using this product
avoid contact with eyes. In case of contact flush eyes with water.

Stop use and ask a doctor if redness or irritation develop and persist for more than 72 hours.

Keep out of reach of children. Children must be supervised in use of this product.

Directions

- pump as needed into your palms and thoroughly spread on both hands.
- rub into skin until dry.

Other Information

- store at 20C-25C (68F to 77F).
- may discolor fabrics.

Inactive Ingredients
Aminomethyl propanol, Carbomer 940, FD&C Blue No. 1 (for winter wonderland scented, apple harvest scented & cherry blossom scented), FD&C Red No. 33 (for winter wonderland scented & apple harvest scented), FD&C Red No. 4(for cherry blossom scented), FD&C Yellow No. 5 (for winter wonderland scented, apple harvest scented & cherry blossom scented), Fragrance, Glycerin, Propylene glycol, Water.